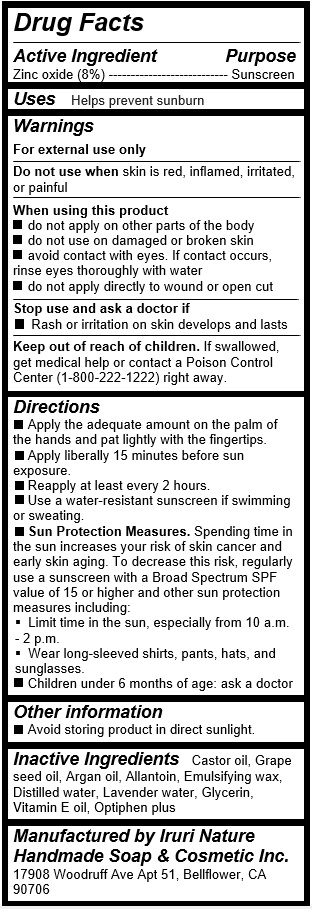 DRUG LABEL: Purple Sunblock
NDC: 71547-111 | Form: CREAM
Manufacturer: Iruri Nature Handmade Soap & Cosmetic Inc
Category: otc | Type: HUMAN OTC DRUG LABEL
Date: 20170725

ACTIVE INGREDIENTS: ZINC OXIDE 1.6 g/20 mL
INACTIVE INGREDIENTS: ARGAN OIL; CASTOR OIL; WATER; GRAPE SEED OIL; ALLANTOIN; GLYCERIN; .ALPHA.-TOCOPHEROL

Purple Sunblock (Grape seed & Argan oil Sunblock)

Active Ingredients

Zinc oxide (8%)

Purpose

Sunscreen

Uses

Helps prevent sunburn

Warnings

For external use only

Do not use when skin is red, inflamed, irritated, or painful

When using this product

- do not apply on other parts of the body

- do not use on damaged or broken skin

- avoid contact with eyes. If contact occurs, rinse eyes thoroughly with water

- do not apply directly to wound or open cut

Stop use and ask a doctor if

- Rash or irritation on skin develops and lasts

Keep out of reach of children

If swallowed, get medical help or contact a Poison Control Center (1-800-222-1222) right away.

Directions

1. Apply the adequate amount on the palm of the hands and pat lightly with the fingertips.

2. Apply liberally 15 minutes before sun exposure.

3. Reapply at least every 2 hours.

4. Use a water-resistant sunscreen if swimming or sweating.

5. Sun Protection Measures. Spending time in the sun increases your risk of skin cancer and early skin aging. To decrease this risk,

regularly use a sunscreen with a Broad Spectrum SPF value of 15 or higher and other sun protection measures including:

1) Limit time in the sun, especially from 10 a.m.- 2 p.m.

2) Wear long-sleeved shirts, pants, hats, and sunglasses.

6. Children under 6 months of age: ask a doctor

Inactive Ingredients

Castor oil, Grape seed oil, Argan oil, Allantoin, Emulsifying wax, Distilled water, Lavender water, Glycerin, Vitamin E oil, Optiphen plus